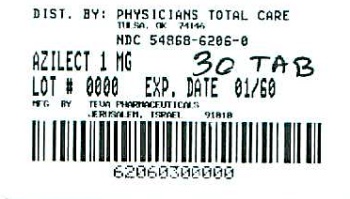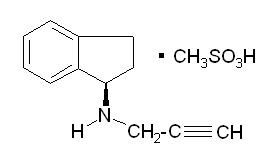 DRUG LABEL: Azilect
NDC: 54868-6206 | Form: TABLET
Manufacturer: Physicians Total Care, Inc.
Category: prescription | Type: HUMAN PRESCRIPTION DRUG LABEL
Date: 20101207

ACTIVE INGREDIENTS: RASAGILINE MESYLATE 1 mg/1 1
INACTIVE INGREDIENTS: MANNITOL; SILICON DIOXIDE; STEARIC ACID; TALC

HIGHLIGHTS OF PRESCRIBING INFORMATION

These highlights do not include all the information needed to use AZILECT® safely and effectively. See full prescribing information for AZILECT®. AZILECT® (rasagiline mesylate) Tablets for Oral Use Initial U.S. Approval: 2006

RECENT MAJOR CHANGES

Dosage and Administration | 12/2009
Contraindications | 12/2009
Warnings and Precautions | 12/2009

1 INDICATIONS AND USAGE

AZILECT is indicated for the treatment of the signs and symptoms of idiopathic Parkinson's disease as initial monotherapy and as adjunct therapy to levodopa. (1)

2 DOSAGE AND ADMINISTRATION

- Monotherapy: AZILECT 1 mg once daily (2.1)
- As adjunct to levodopa: AZILECT 0.5 mg once daily. Dose increase to 1 mg daily as required for sufficient clinical response. (2.2)
- Patients with mild hepatic impairment: AZILECT 0.5 mg once daily should not be exceeded. AZILECT should not be used in patients with moderate or severe hepatic impairment (2.3)
- AZILECT has not been studied in patients with severe renal impairment (2.4)
- Patients taking ciprofloxacin or other CYP1A2 inhibitors: AZILECT 0.5 mg once daily should not be exceeded. (2.5)

3 DOSAGE FORMS AND STRENGTHS

- AZILECT 0.5 mg tablets (containing, as the active ingredient, rasagiline mesylate equivalent to 0.5 mg of rasagiline base) (3)
- AZILECT 1 mg tablets (containing, as the active ingredient, rasagiline mesylate equivalent to 1 mg of rasagiline base) (3)

4 CONTRAINDICATIONS

- Concomitant use of : -meperidine, tramadol, methadone or propoxyphene (4.1)-dextromethorphan, St. John's wort or cyclobenzaprine (4.2)-other MAO inhibitors (selective or non-selective) (4.3)

5 WARNINGS AND PRECAUTIONS

- Risk of severe CNS toxicity (serotonin syndrome) when AZILECT is combined with antidepressants. (5.1)
- Concomitant use of ciprofloxacin or other CYP1A2 inhibitors: Increase in rasagiline plasma concentrations. 0.5 mg rasagiline once daily should not be exceeded (5.2)
- Patients with hepatic impairment: Increase in rasagiline plasma concentrations. Limit dose to 0.5 mg rasagiline in mild hepatic impairment. AZILECT should not be used in patients with moderate or severe hepatic impairment (5.3)
- Risk for Hypertensive Crisis and nonselective MAO inhibition above the recommended Doses (5.4)
- Melanoma (5.4)
- AZILECT may cause lower blood pressure, especially postural hypotension (5.7) or increase blood pressure in different patients (5.8)
- AZILECT may cause or exacerbate hallucinations or potentially other manifestations of psychotic-like behavior (5.9)

6 ADVERSE REACTIONS

- Most common adverse reactions (treatment difference ≥ 3% greater than placebo); with monotherapy: flu syndrome, arthralgia, depression, dyspepsia. (6.1)
- Most common adverse reactions (treatment difference ≥ 3% greater than placebo); when used as adjunct to levodopa: dyskinesia, accidental injury, weight loss, postural hypotension, vomiting, anorexia, arthralgia, abdominal pain, nausea, constipation, dry mouth, rash, abnormal dreams, fall. (6.1)

To report SUSPECTED ADVERSE REACTIONS, contact TEVA at 1-800-221-4026 or FDA at 1-800-FDA-1088 or www.fda.gov/medwatch.

7 DRUG INTERACTIONS

- Meperidine: Risk of serious, sometimes fatal reactions from serotonin syndrome. See also Contraindications. (7.1)
- Dextromethorphan: Risk of psychosis episodes or bizarre behavior. See also Contraindications. (7.2)
- MAO inhibitors: Risk of non-selective MAO inhibition and hypertensive crisis. See also Contraindications. (7.4)
- Antidepressants (SSRIs, SNRIs, tricyclic, tetracyclic, or triazolopyridine): Concomitant use not recommended. (7.5)
- Levodopa: See also Warnings and Precautions. (7.6)
- Ciprofloxacin and Other CYP1A2 Inhibitors: Increased rasagiline plasma levels possible. Increased risk of adverse events. See also Dosage and Administration and Warnings and Precautions.(7.7)

8 USE IN SPECIFIC POPULATIONS

- Pregnancy: AZILECT should be used only if the potential benefit justifies the potential risk to the fetus. (8.1)
- Nursing mothers: Rasagiline inhibits prolactin secretion and may inhibit milk secretion. It is not known whether rasagiline is excreted in human milk. Use with caution. (8.3)
- Hepatic impairment: Rasagiline plasma concentrations may be increased. See also Dosage and Administration and Warnings and Precautions. (8.6)

FULL PRESCRIBING INFORMATION

RECENT MAJOR CHANGES

Enter section text here

1 INDICATIONS AND USAGE

AZILECT (rasagiline tablets) is indicated for the treatment of the signs and symptoms of idiopathic Parkinson's disease as initial monotherapy and as adjunct therapy to levodopa.

The effectiveness of AZILECT was demonstrated in patients with early Parkinson's disease who were receiving AZILECT as monotherapy and who were not receiving any concomitant dopaminergic therapy. The effectiveness of AZILECT as adjunct therapy was demonstrated in patients with Parkinson's disease who were treated with levodopa.

2 DOSAGE AND ADMINISTRATION

AZILECT is a selective inhibitor of monoamine oxidase (MAO)-B at recommended doses of 0.5 or 1 mg daily. Dietary tyramine restriction is not ordinarily required with recommended doses of AZILECT. However, certain foods (e.g., aged cheeses, such as Stilton cheese) may contain very high amounts (i.e., > 150 mg) of tyramine and could potentially cause a hypertensive "cheese" reaction in patients taking AZILECT even at the recommended dose due to mild increased sensitivity to tyramine. The selectivity for inhibiting MAO-B diminishes in a dose-related manner as the dose is progressively increased above the recommended daily dose [see Warnings and Precautions (5.4), Clinical Pharmacology (12.3, and Information for Patients (17.3))].

2.1 Monotherapy

The recommended AZILECT dose for the treatment of Parkinson's disease patients is 1 mg administered orally once daily.

2.2 Adjunctive Therapy

The recommended initial dose is 0.5 mg administered orally once daily. If a sufficient clinical response is not achieved, the dose may be increased to 1 mg administered once daily.

Change of Levodopa Dose in Adjunct Therapy

When AZILECT is used in combination with levodopa, a reduction of the levodopa dosage may be considered based upon individual response. During the controlled trials of AZILECT as adjunct therapy to levodopa, levodopa dosage was reduced in some patients. In clinical studies, dosage reduction of levodopa was allowed within the first 6 weeks if dopaminergic side effects, including dyskinesia and hallucinations, emerged. In Study 1, levodopa dosage reduction occurred in 8% of patients in the placebo group and in 16% and 17% of patients in the 0.5 mg/day and 1 mg/day rasagiline groups, respectively. In those patients who had levodopa dosage reduced, the dose was reduced on average by about 7%, 9%, and 13% in the placebo, 0.5 mg/day, and 1 mg/day groups, respectively. In Study 2, levodopa dosage reduction occurred in 6% of patients in the placebo group and in 9% in the rasagiline 1 mg/day group. In patients who had their levodopa dosage reduced, the dose was reduced on average by about 13% and 11% in the placebo and the rasagiline groups, respectively.

2.3 Patients with Hepatic Impairment

AZILECT plasma concentrations will increase in patients with hepatic impairment. Patients with mild hepatic impairment should use 0.5 mg daily of AZILECT. AZILECT should not be used in patients with moderate or severe hepatic impairment [see Warnings and Precautions (5.3), Use in Specific Populations (8.6), and Clinical Pharmacology (12.3)].

2.4 Patients with Renal Impairment

Dose adjustment of AZILECT is not required for patients with mild or moderate renal impairment because AZILECT plasma concentrations are not increased in patients with moderate renal impairment. Rasagiline has not been studied in patients with severe renal impairment.

2.5 Patients Taking Ciprofloxacin or Other CYP1A2 Inhibitors

Rasagiline plasma concentrations are expected to double in patients taking concomitant ciprofloxacin and other CYP1A2 inhibitors. Therefore, patients taking concomitant ciprofloxacin or other CYP1A2 inhibitors should use 0.5 mg daily of AZILECT [see Warnings and Precautions (5.2), Drug Interactions (7.7), and Clinical Pharmacology (12.3)].

3 DOSAGE FORMS AND STRENGTHS

AZILECT 0.5 mg Tablets: White to off-white, round, flat, beveled tablets, debossed with "GIL 0.5" on one side and plain on the other side containing, as the active ingredient, rasagiline mesylate equivalent to 0.5 mg of rasagiline base.

AZILECT 1 mg Tablets: White to off-white, round, flat, beveled tablets, debossed with "GIL 1" on one side and plain on the other side containing, as the active ingredient, rasagiline mesylate equivalent to 1 mg of rasagiline base.

4 CONTRAINDICATIONS

Enter section text here

4.1 Meperidine and Certain Other Analgesics

AZILECT is contraindicated for use with meperidine. Serious adverse reactions have been precipitated with concomitant use of meperidine (e.g., Demerol and other tradenames) and MAO inhibitors (MAOIs) including selective MAO-B inhibitors. These adverse reactions are often described as "serotonin syndrome", a potentially serious condition, which can result in death. Typical clinical signs and symptoms include behavioral and cognitive/mental status changes (e.g., confusion, hypomania, hallucinations, agitation, delirium, headache, and coma), autonomic effects (e.g., syncope, shivering, sweating, high fever/hyperthermia, hypertension, hypotension, tachycardia, nausea, diarrhea), and somatic effects (e.g., muscular rigidity, myoclonus, muscle twitching, hyperreflexia manifested by clonus, and tremor). At least 14 days should elapse between discontinuation of AZILECT and initiation of treatment with meperidine.
For similar reasons, AZILECT should not be administered with the analgesic agents tramadol, methadone, and propoxyphene.
In the post-marketing period, serotonin syndrome has been reported in a patient erroneously treated with a higher than recommended dose of AZILECT (4 mg daily) and tramadol.

4.2 Other Drugs

AZILECT should not be used with the antitussive agent dextromethorphan. The combination of MAO inhibitors and dextromethorphan has been reported to cause brief episodes of psychosis or bizarre behavior. AZILECT is also contraindicated for use with St. John's wort, and cyclobenzaprine (a tricyclic muscle relaxant).

4.3 MAO Inhibitors

AZILECT should not be administered along with any other MAO inhibitor (selective or non-selective) because of the increased risk of non-selective MAO inhibition that may lead to a hypertensive crisis. At least 14 days should elapse between discontinuation of AZILECT and initiation of treatment with any MAO inhibitor.

5 WARNINGS AND PRECAUTIONS

Enter section text here

5.1 Coadministration with Antidepressants

Severe CNS toxicity associated with hyperpyrexia has been reported with the combined treatment of an antidepressant (e.g., selective serotonin reuptake inhibitors-SSRIs, serotonin-norepinephrine reuptake inhibitors-SNRIs, tricyclic antidepressants, tetracyclic antidepressants, triazolopyridine antidepressants) and a non-selective MAOI (e.g., phenelzine, tranylcypromine) or selective MAO-B inhibitors, such as selegiline (Eldepryl) and rasagiline (AZILECT). These adverse reactions are often described as "serotonin syndrome" which can result in death. In the post-marketing period, non-fatal cases of serotonin syndrome have been reported in patients treated with antidepressants concomitantly with AZILECT.

The symptoms of serotonin syndrome have included behavioral and cognitive/mental status changes (e.g., confusion, hypomania, hallucinations, agitation, delirium, headache, and coma), autonomic effects (e.g., syncope, shivering, sweating, high fever/hyperthermia, hypertension, tachycardia, nausea, diarrhea), and somatic effects (e.g., muscular rigidity, myoclonus, muscle twitching, hyperreflexia manifested by clonus, and tremor).

AZILECT clinical trials did not allow concomitant use of fluoxetine or fluvoxamine with AZILECT, but the following antidepressants and doses were allowed in the AZILECT trials: amitriptyline ≤ 50 mg/daily, trazodone ≤ 100 mg/daily, citalopram ≤ 20 mg/daily, sertraline ≤ 100 mg/daily and paroxetine ≤ 30 mg/daily.

Although a small number of rasagiline-treated patients were concomitantly exposed to antidepressants (tricyclics n=115; SSRIs n=141), the exposure, both in dose and number of subjects, was not adequate to rule out the possibility of an untoward reaction from combining these agents. Furthermore, because the mechanisms of these reactions are not fully understood, it seems prudent, in general, to avoid the combination of AZILECT with any antidepressant. At least 14 days should elapse between discontinuation of AZILECT and initiation of treatment with a SSRI, SNRI, tricyclic, tetracyclic, or triazolopyridine antidepressant. Because of the long half lives of certain antidepressants (e.g., fluoxetine and its active metabolite), at least five weeks (perhaps longer, especially if fluoxetine has been prescribed chronically and/or at higher doses) should elapse between discontinuation of fluoxetine and initiation of AZILECT [see Drug Interactions (7.5)].

5.2 Ciprofloxacin and Other CYP1A2 Inhibitors

Rasagiline plasma concentrations may increase up to 2 fold in patients using concomitant ciprofloxacin and other CYP1A2 inhibitors [see Dosage and Administration (2.5), Drug Interactions (7.7), and Clinical Pharmacology (12.3)].

5.3 Hepatic Impairment

Rasagiline plasma concentration may increase in patients with mild (up to 2 fold, Child-Pugh score 5-6), moderate (up to 7 fold, Child-Pugh score 7-9), and severe (Child-Pugh score 10-15) hepatic impairment. Patients with mild hepatic impairment should be given the dose of 0.5 mg/day. AZILECT should not be used in patients with moderate or severe hepatic impairment [see Dosage and Administration (2.3) and Clinical Pharmacology (12.3)].

5.4 Risk for Hypertensive Crisis and Nonselective Monoamine Oxidase Inhibition Above The Recommended Doses

AZILECT is a selective inhibitor of monoamine oxidase (MAO)-B at the recommended doses of 0.5 or 1 mg daily. AZILECT should not be used at daily doses exceeding 1 mg/day (or 0.5 mg/day for patients with mild hepatic impairment or in patients using concomitant ciprofloxacin or another CYP1A2 inhibitor) because of the risks of hypertensive crisis and other adverse reactions associated with nonselective inhibition of MAO [see Dosage and Administration (2), Drug Interactions (7.9), and Clinical Pharmacology (12.3)].

Dietary tyramine restriction is not ordinarily required with ingestion of most foods and beverages that may contain tyramine, during treatment with recommended doses of AZILECT. However, certain foods (e.g., aged cheeses, such as Stilton cheese) may contain very high amounts (i.e., > 150 mg) of tyramine and could potentially cause a hypertensive "cheese" reaction in patients taking AZILECT even at the recommended doses due to mild increased sensitivity to tyramine. Patients should be advised to avoid foods (e.g., aged cheese) containing a very large amount of tyramine while taking recommended doses of AZILECT because of the potential for large increases in blood pressure. Selectivity for inhibiting MAO-B diminishes in a dose-related manner as the dose is progressively increased above the recommended daily doses.

There were no cases of hypertensive crisis in the clinical development program associated with 1 mg daily rasagiline treatment, in which most patients did not follow dietary tyramine restriction.

Rare cases of hypertensive crisis have been reported in the post-marketing period in patients after ingesting unknown amounts of tyramine-rich foods while taking recommended doses of AZILECT.

5.5 Melanoma

Epidemiological studies have shown that patients with Parkinson's disease have a higher risk (2- to approximately 6-fold higher) of developing melanoma than the general population. Whether the increased risk observed was due to Parkinson's disease or other factors, such as drugs used to treat Parkinson's disease, is unclear.

For the reasons stated above, patients and providers are advised to monitor for melanomas frequently and on a regular basis. Ideally, periodic skin examinations should be performed by appropriately qualified individuals (e.g., dermatologists).

5.6 Dyskinesia

When used as an adjunct to levodopa, AZILECT may cause dyskinesia or potentiate dopaminergic side effects and exacerbate pre-existing dyskinesia (treatment-emergent dyskinesia occurred in about 18% of patients treated with 0.5 mg or 1 mg rasagiline as an adjunct to levodopa, and 10% of patients who received placebo as an adjunct to levodopa). Decreasing the dose of levodopa may ameliorate this side effect.

5.7 Lowering of Blood Pressure and Postural/Orthostatic Hypotension

In placebo controlled studies of AZILECT given in combination with levodopa, the incidence of postural hypotension consisting of a systolic blood pressure decrease (> 30 mm Hg) or a diastolic blood pressure decrease (> 20 mm Hg) after standing was 13.4 % with AZILECT (1 mg/day) compared to 8.5 % with placebo.

At the 1 mg dose, the frequency of orthostatic hypotension at any time during the study was approximately 44 % for AZILECT vs 33% for placebo for mild to moderate systolic blood pressure decrements (> 20 mm Hg), 40 % for AZILECT vs 33 % for placebo for mild to moderate diastolic blood pressure decrements (> 10 mm Hg), 7 % for AZILECT vs 3 % for placebo for severe systolic blood pressure decrements (> 40 mm Hg), and 9 % for AZILECT vs 6 % for placebo for severe diastolic blood pressure decrements (> 20 mm Hg). There was also an increased risk for some of these abnormalities at the lower 0.5 mg daily dose and for an individual patient having mild to moderate or severe postural hypotension for both systolic and diastolic blood pressure.

Clinical trial data further suggest that postural hypotension occurs most frequently in the first two months of AZILECT treatment and tends to decrease over time.

Some patients treated with AZILECT experienced a mildly increased risk for significant decreases in blood pressure unrelated to standing but while supine.

The risk for post-treatment hypotension (e.g., systolic < 90 or diastolic < 50 mm Hg) combined with a significant decrease from baseline (e.g., systolic > 30 or diastolic > 20 mm Hg) was higher for AZILECT 1 mg (3.2 %) compared to placebo (1.3 %).

There was no clear increased risk for lowering of blood pressure or postural hypotension associated with AZILECT 1 mg/day as monotherapy.

When used as an adjunct to levodopa, postural hypotension was also reported as an adverse reaction in approximately 6% of patients treated with 0.5 mg rasagiline, 9% of patients treated with 1 mg rasagiline and 3% of patients treated with placebo. Postural hypotension led to drug discontinuation and premature withdrawal from clinical trials in one (0.7%) patient treated with rasagiline 1 mg/day, no patients treated with rasagiline 0.5 mg/day and no placebo-treated patients.

5.8 Elevation of Blood Pressure

In studies in which AZILECT (1 mg/day) was given in conjunction with levodopa, AZILECT produced an increased incidence of a significant, high blood pressure (e.g., systolic > 180 or diastolic > 100 mm Hg) of 4% compared to 3% for placebo.

The risk for developing post-treatment high blood pressure (e.g., systolic > 180 or diastolic >100 mm Hg) combined with a significant increase from baseline (e.g., systolic > 30 or diastolic > 20 mm Hg) was higher for AZILECT (2 %) compared to placebo (1 %).

There was no increased frequency of the incidence of hypertension as an adverse reaction in the adjunctive treatment pivotal trials for AZILECT treatment vs placebo.

There was no observed increased risk for increasing blood pressure or high blood pressure (based upon various measurements and analyses) or for the development of hypertension as an adverse reaction in the monotherapy study for 1 mg daily AZILECT treatment (vs placebo).

5.9 Hallucinations / Psychotic-Like Behavior

In the monotherapy study, hallucinations were reported as an adverse event in 1.3% of patients treated with 1 mg rasagiline and in 0.7% of patients treated with placebo. In the monotherapy trial, hallucinations led to drug discontinuation and premature withdrawal from clinical trials in 1.3% of the 1 mg rasagiline-treated patients and in none of the placebo-treated patients.

When used as an adjunct to levodopa, hallucinations were reported as an adverse reaction in approximately 5% of patients treated with 0.5 mg/day AZILECT, 4% of patients treated with 1 mg/day AZILECT and 3% of patients treated with placebo. Hallucinations led to drug discontinuation and premature withdrawal from clinical trials in about 1% of patients treated with 0.5 mg/day or 1 mg/day rasagiline and none of the placebo-treated patients.

Patients should be informed of the possibility of developing hallucinations and instructed to report them to their health care provider promptly should they develop.

Patients with a major psychotic disorder should ordinarily not be treated with AZILECT because of the risk of exacerbating the psychosis with an increase in central dopaminergic tone. In addition, many treatments for psychosis that decrease in central dopaminergic tone may decrease the effectiveness of AZILECT.

AZILECT administration may cause or exacerbate psychotic-like behavior based upon post-marketing reports. This adverse reaction has been reported with many anti-Parkinsonian drugs that increase central dopaminergic tone. This abnormal behavior has been exhibited by one or more of a variety of manifestations including paranoia, confusional state/confusion, psychotic disorder, agitation, delusion, and hallucinations.

5.10 Withdrawal-Emergent Hyperpyrexia and Confusion

A symptom complex resembling neuroleptic malignant syndrome (characterized by elevated temperature, muscular rigidity, altered consciousness, and autonomic instability), with no other obvious etiology, has been reported in association with rapid dose reduction, withdrawal of, or changes in drugs that increase central dopaminergic tone. [see Dosage and Administration (2.2)].

Withdrawal emergent hyperpyrexia was not reported in the AZILECT clinical development program.

5.11 Laboratory Tests

No specific laboratory tests are required for the treatment of patients on AZILECT.

6 ADVERSE REACTIONS

Enter section text here

6.1 Clinical Studies Experience

During the clinical development of AZILECT, 1361 Parkinson's disease patients received rasagiline as initial monotherapy or as adjunct therapy to levodopa. As these two populations differ, not only in the adjunct use of levodopa during rasagiline treatment, but also in the severity and duration of their disease, they may have differential risks for various adverse reactions. Therefore, most of the adverse reactions data in this section are presented separately for each population.

Because clinical trials are conducted under widely varying conditions, adverse reaction rates observed in the clinical trials of a drug cannot be directly compared to rates in the clinical trials of another drug and may not reflect the rates of adverse reactions observed in practice.

Patients Receiving AZILECT as Initial Monotherapy Treatment

Adverse Reactions Leading to Discontinuation in Controlled Clinical Studies

In the double-blind, placebo-controlled trials conducted in patients receiving AZILECT as monotherapy, approximately 5% of the 149 patients treated with rasagiline discontinued treatment due to adverse reactions compared to 2% of the 151 patients who received placebo.

The only adverse reaction that led to the discontinuation of more than one patient was hallucinations.

Adverse Reaction Incidence in Controlled Clinical Studies

The most commonly observed adverse reactions were those in which the treatment difference for the incidence in AZILECT-treated patients was ≥ 3 % greater than the incidence in the placebo-treated patients and included flu syndrome, arthralgia, depression, and dyspepsia. Table 1 lists treatment-emergent adverse reactions that occurred in ≥ 2% of patients receiving AZILECT as monotherapy participating in the double-blind, placebo-controlled trial and were numerically more frequent than in the placebo group.

Table 1. Treatment-Emergent* Adverse Reactions in AZILECT 1 mg-Treated Monotherapy Patients
Placebo-Controlled Studies Without Levodopa Treatment | AZILECT 1 mg (N=149) | Placebo (N=151)
 | % of Patients | % of Patients
Headache | 14 | 12
Arthralgia | 7 | 4
Dyspepsia | 7 | 4
Depression | 5 | 2
Fall | 5 | 3
Flu syndrome | 5 | 1
Conjunctivitis | 3 | 1
Fever | 3 | 1
Gastroenteritis | 3 | 1
Rhinitis | 3 | 1
Arthritis | 2 | 1
Ecchymosis | 2 | 0
Malaise | 2 | 0
Neck Pain | 2 | 0
Paresthesia | 2 | 1
Vertigo | 2 | 1

*Incidence ≥ 2% in AZILECT 1 mg group and numerically more frequent than in placebo group

Other events of potential clinical importance reported by 1% or more of patients receiving AZILECT as monotherapy, and at least as frequent as in the placebo group, in descending order of frequency include: dizziness, diarrhea, chest pain, albuminuria, allergic reaction, alopecia, angina pectoris, anorexia, asthma, hallucinations, impotence, leukopenia, libido decreased, liver function tests abnormal, skin carcinoma, syncope, vesiculobullous rash, vomiting.

There were no significant differences in the safety profile based on age or gender.

Patients Receiving AZILECT as Adjunct to Levodopa Therapy

Adverse Reactions Leading to Discontinuation in Controlled Clinical Studies

In a double-blind, placebo-controlled trial (Study 1) conducted in patients treated with AZILECT as adjunct to levodopa therapy, approximately 9% of the 164 patients treated with AZILECT 0.5 mg/day and 7% of the 149 patients treated with AZILECT 1 mg/day discontinued treatment due to adverse reactions compared to 6% of the 159 patients who received placebo. The adverse reactions that led to discontinuation of more than one rasagiline-treated patient were: diarrhea, weight loss, hallucination, and rash. Adverse event reporting was considered more reliable for Study 1 than for the second controlled trial (Study 2); therefore only the adverse event data from Study 1 are presented in this section of labeling.

Adverse Reactions: Incidence in Controlled Clinical Studies

The most commonly observed adverse reactions were those in which the treatment difference for the incidence in AZILECT-treated patients (n=149) was ≥ 3 % greater than the incidence in the placebo-treated patients (n=159) and included dyskinesia, accidental injury, weight loss, postural hypotension, vomiting, anorexia, arthralgia, abdominal pain, nausea, constipation, dry mouth, rash, abnormal dreams, and fall.

Table 2 lists treatment-emergent adverse reactions that occurred in ≥ 2% of patients treated with AZILECT 1 mg/day as adjunct to levodopa therapy participating in the double-blind, placebo-controlled trial (Study 1) and that were numerically more frequent than the placebo group. The table also shows the rates for the 0.5 mg group in Study 1.

Table 2. Incidence of Treatment-Emergent* Adverse Reactions in Patients Receiving AZILECT as Adjunct to Levodopa Therapy in Study 1
 | AZILECT 1 mg + Levodopa (N=149) | AZILECT 0.5 mg + Levodopa (N=164) | Placebo + Levodopa (N=159)
 | % of patients | % of patients | % of patients
Dyskinesia | 18 | 18 | 10
Accidental injury | 12 | 8 | 5
Nausea | 12 | 10 | 8
Headache | 11 | 8 | 10
Fall | 11 | 12 | 8
Weight loss | 9 | 2 | 3
Constipation | 9 | 4 | 5
Postural hypotension | 9 | 6 | 3
Arthralgia | 8 | 6 | 4
Vomiting | 7 | 4 | 1
Dry mouth | 6 | 2 | 3
Rash | 6 | 3 | 3
Somnolence | 6 | 4 | 4
Abdominal pain | 5 | 2 | 1
Anorexia | 5 | 2 | 1
Diarrhea | 5 | 7 | 4
Ecchymosis | 5 | 2 | 3
Dyspepsia | 5 | 4 | 4
Paresthesia | 5 | 2 | 3
Abnormal dreams | 4 | 1 | 1
Hallucinations | 4 | 5 | 3
Ataxia | 3 | 6 | 1
Dyspnea | 3 | 5 | 2
Infection | 3 | 2 | 2
Neck pain | 3 | 1 | 1
Sweating | 3 | 2 | 1
Tenosynovitis | 3 | 1 | 0
Dystonia | 3 | 2 | 1
Gingivitis | 2 | 1 | 1
Hemorrhage | 2 | 1 | 1
Hernia | 2 | 1 | 1
Myasthenia | 2 | 2 | 1

*Incidence ≥ 2% in AZILECT 1 mg group and numerically more frequent than in placebo group

Several of the more common adverse reactions seemed dose-related, including weight loss, postural hypotension, and dry mouth.

Other adverse reactions of potential clinical importance reported in Study 1 by 1% or more of patients treated with rasagiline 1 mg/day as adjunct to levodopa therapy, and at least as frequent as in the placebo group, in descending order of frequency include : skin carcinoma, anemia, albuminuria, amnesia, arthritis, bursitis, cerebrovascular accident, confusion, dysphagia, epistaxis, leg cramps, pruritus, skin ulcer.

There were no significant differences in the safety profile based on age or gender.

Other Adverse Reactions Observed During All Phase 2/3 Clinical Trials

Rasagiline was administered to approximately 1361 patients during all PD phase 2/3 clinical trials. About 283 patients received rasagiline for at least one year, approximately 410 patients received rasagiline for at least two years, 116 patients received rasagiline for at least 3 years, and 245 patients received rasagiline for more than 3 years, with some patients treated for more than 5 years. The long-term safety profile was similar to that observed with shorter duration exposure.

The frequencies listed below represent the proportion of the 1361 individuals exposed to rasagiline who experienced events of the type cited.

All events that occurred at least twice (or once for serious or potentially serious events), except those already listed above, trivial events, terms too vague to be meaningful, adverse events with no plausible relation to treatment, and events that would be expected in patients of the age studied, were reported without regard to determination of a causal relationship to rasagiline.

Events are further classified within body system categories and enumerated in order of decreasing frequency using the following definitions: frequent adverse events are defined as those occurring in at least 1/100 patients, infrequent adverse events are defined as those occurring in at least 1/100 to 1/1000 patients and rare adverse events are defined as those occurring in fewer than 1/1000 patients.

Body as a whole: Frequent: asthenia Infrequent: chills, face edema, flank pain, photosensitivity reaction

Cardiovascular system: Frequent: bundle branch block Infrequent: deep thrombophlebitis, heart failure, migraine, myocardial infarct, phlebitis, ventricular tachycardia Rare: arterial thrombosis, atrial arrhythmia, AV block complete, AV block second degree, bigeminy, cerebral hemorrhage, cerebral ischemia, ventricular fibrillation

Digestive system: Frequent: gastrointestinal hemorrhage Infrequent: colitis, esophageal ulcer, esophagitis, fecal incontinence, intestinal obstruction, mouth ulceration, stomach ulcer, stomatitis, tongue edema Rare: hematemesis, hemorrhagic gastritis, intestinal perforation, intestinal stenosis, jaundice, large intestine perforation, megacolon, melena

Hemic and Lymphatic system: Infrequent: macrocytic anemia Rare: purpura, thrombocythemia

Metabolic and Nutritional disorders: Infrequent: hypocalcemia

Musculoskeletal system: Infrequent: bone necrosis, muscle atrophy Rare: arthrosis

Nervous system: Frequent: abnormal gait, anxiety, hyperkinesia, hypertonia, neuropathy, tremor Infrequent: agitation, aphasia, circumoral paresthesia, convulsion, delusions, dementia, dysarthria, dysautonomia, dysesthesia, emotional lability, facial paralysis, foot drop, hemiplegia, hypesthesia, incoordination, manic reaction, myoclonus, neuritis, neurosis, paranoid reaction, personality disorder, psychosis, wrist drop Rare: apathy, delirium, hostility, manic depressive reaction, myelitis, neuralgia, psychotic depression, stupor

Respiratory system: Frequent: cough increased Infrequent: apnea, emphysema, laryngismus, pleural effusion, pneumothorax Rare: interstitial pneumonia, larynx edema, lung fibrosis

Skin and Appendages: Infrequent: eczema, urticaria Rare: exfoliative dermatitis, leukoderma

Special senses: Infrequent: blepharitis, deafness, diplopia, eye hemorrhage, eye pain, glaucoma, keratitis, ptosis, retinal degeneration, taste perversion, visual field defect Rare: blindness, parosmia, photophobia, retinal detachment, retinal hemorrhage, strabismus, taste loss, vestibular disorder

Urogenital system: Frequent: hematuria, urinary incontinence Infrequent: acute kidney failure, dysmenorrhea, dysuria, kidney calculus, nocturia, polyuria, scrotal edema, sexual function abnormal, urinary retention, urination impaired, vaginal hemorrhage, vaginal moniliasis, vaginitis Rare: abnormal ejaculation, amenorrhea, anuria, epididymitis, gynecomastia, hydroureter, leukorrhea, priapism

6.2 Post-marketing Experience

The following adverse events not described in sections 4 and 5 have been identified during the post-marketing/post-approval use of AZILECT. Because these adverse events are reported voluntarily from a population of uncertain size, it is not possible to reliably estimate their frequency nor to establish unequivocally a causal relationship to drug exposure: Increased libido including hypersexuality, impulse control symptoms, pathological gambling [see Patient Counseling Information (17.11)]

7 DRUG INTERACTIONS

Enter section text here

7.1 Meperidine

Serious, sometimes fatal reactions have been precipitated with concomitant use of meperidine (e.g., Demerol and other tradenames) and MAO inhibitors including selective MAO-B inhibitors [see Contraindications (4.1)].

7.2 Dextromethorphan

The concomitant use of AZILECT and dextromethorphan was not allowed in clinical studies. The combination of MAO inhibitors and dextromethorphan has been reported to cause brief episodes of psychosis or bizarre behavior. Therefore, in view of AZILECT's MAO inhibitory activity, dextromethorphan should not be used concomitantly with AZILECT [see Contraindications (4.2)].

7.3 Sympathomimetic Medications

The concomitant use of AZILECT and sympathomimetic medications was not allowed in clinical studies. Severe hypertensive reactions have followed the administration of sympathomimetics and non-selective MAO inhibitors. One case of hypertensive crisis has been reported in a patient taking the recommended dose of a selective MAO-B inhibitor and a sympathomimetic medication (ephedrine). Elevated blood pressure was reported in another patient taking the recommended dose of AZILECT and ophthalmic drops with a sympathomimetic medication (tetrahydrozoline).

Because AZILECT is a selective MAOI, hypertensive reactions are not ordinarily expected with the concomitant use of sympathomimetic medications. Nevertheless, caution should be exercised when concomitantly using recommended doses of AZILECT with any sympathomimetic medications including nasal, oral, and ophthalmic decongestants and cold remedies.

7.4 MAO Inhibitors

AZILECT should not be administered along with other MAO inhibitors because of the increased risk of non-selective MAO inhibition that may lead to a hypertensive crisis [see Contraindications (4.3)].

7.5 Antidepressants

Concomitant use of AZILECT with one of many classes of antidepressants (e.g., SSRIs, SNRIs, triazolopyridine, tricyclic or tetracyclic antidepressants) is not recommended [see Warnings and Precautions (5.1)].

7.6 Levodopa/Carbidopa

[see Warnings and Precautions (5.6) and Clinical Pharmacology (12.3)].

7.7 Ciprofloxacin and Other CYP1A2 Inhibitors

Rasagiline plasma concentrations may increase up to 2 fold in patients using concomitant ciprofloxacin and other CYP1A2 inhibitors. This could result in increased adverse events [see Warnings and Precautions (5.2) and Clinical Pharmacology (12.3)].

7.8 Theophylline

[see Clinical Pharmacology (12.3)].

7.9 Tyramine/Rasagiline Interaction

MAO in the gastrointestinal tract and liver (primarily type A) is thought to provide vital protection from exogenous amines (e.g., tyramine) that have the capacity, if absorbed intact, to cause a "hypertensive crisis," the so-called "cheese reaction". If large amounts of certain exogenous amines (e.g., from fermented cheese, herring, over-the-counter cough/cold medications) gain access to the systemic circulation because MAO-A has been inhibited, they cause release of norepinephrine which may result in a rise in systemic blood pressure. MAOIs that selectively inhibit MAO-B are largely devoid of the potential to cause tyramine-induced hypertensive crisis.

Results of a special tyramine challenge study indicate that rasagiline is selective for MAO-B at recommended doses and can ordinarily be used without dietary tyramine restriction. However, certain foods (e.g., aged cheeses, such as Stilton cheese) may contain very high amounts (i.e., > 150 mg) of tyramine and could potentially cause a hypertensive cheese reaction in patients taking AZILECT due to mild increased sensitivity to tyramine. Patients should be advised to avoid foods (e.g., aged cheese) containing a very large amount of tyramine while taking recommended doses of AZILECT because of the potential for large increases in blood pressure. Selectivity for inhibiting MAO-B diminishes in a dose-related manner as the dose is progressively increased above the recommended daily doses.

There were no cases of hypertensive crisis in the clinical development program associated with 1 mg daily rasagiline treatment, in which most patients did not follow dietary tyramine restriction.

Despite the selective inhibition of MAO-B at recommended doses of AZILECT, there have been post-marketing reports of patients who experienced significantly elevated blood pressure (including rare cases of hypertensive crisis) after ingestion of unknown amounts of tyramine-rich foods while taking recommended doses of AZILECT [see Dosing and Administration (2), and Warnings and Precautions (5.4)].

8 USE IN SPECIFIC POPULATIONS

Enter section text here

8.1 Pregnancy

Category C

No effect on embryo-fetal development was observed in a combined mating/fertility and embryo-fetal development study in female rats at doses up to 3 mg/kg/day (approximately 30 times the expected plasma rasagiline exposure (AUC) at the maximum recommended human dose [MRHD, 1 mg/day]). Effects on embryo-fetal development in rabbit have not been adequately assessed.

In a study in which pregnant rats were dosed with rasagiline (0.1, 0.3, 1 mg/kg/day) orally, from the beginning of organogenesis to day 20 post-partum, offspring survival was decreased and offspring body weight was reduced at doses of 0.3 mg/kg/day and 1 mg/kg/day (10 and 16 times the expected plasma rasagiline exposure [AUC] at the MRHD). No plasma data were available at the no-effect dose (0.1 mg/kg); however, that dose is 1 times the MRHD on a mg/m^2 basis. Rasagiline's effect on physical and behavioral development was not adequately assessed in this study.

Rasagiline may be given as an adjunct therapy to levodopa/carbidopa treatment. In a study in which pregnant rats were dosed with rasagiline (0.1, 0.3, 1 mg/kg/day) and levodopa/carbidopa (80/20 mg/kg/day) (alone and in combination) throughout the period of organogenesis, there was an increased incidence of wavy ribs in fetuses from rats treated with rasagiline in combination with levodopa/carbidopa at 1/80/20 mg/kg/day (approximately 8 times the plasma AUC expected in humans at the MRHD and 1/1 times the MRHD of levodopa/carbidopa [800/200 mg/day] on a mg/m^2 basis). In a study in which pregnant rabbits were dosed throughout the period of organogenesis with rasagiline alone (3 mg/kg) or in combination with levodopa/carbidopa (rasagiline: 0.1, 0.6, 1.2 mg/kg, levodopa/carbidopa: 80/20 mg/kg/day), an increase in embryo-fetal death was noted at rasagiline doses of 0.6 and 1.2 mg/kg/day when administered in combination with levodopa/carbidopa (approximately 7 and 13 times, respectively, the plasma rasagiline AUC at the MRHD). There was an increase in cardiovascular abnormalities with levodopa/carbidopa alone (1/1 times the MRHD on a mg/m^2 basis) and to a greater extent when rasagiline (at all doses; 1-13 times the plasma rasagiline AUC at the MRHD) was administered in combination with levodopa/carbidopa.

There are no adequate and well-controlled studies of rasagiline in pregnant women. Therefore, AZILECT should be used during pregnancy only if the potential benefit justifies the potential risk to the fetus.

8.3 Nursing Mothers

In rats rasagiline was shown to inhibit prolactin secretion and it may inhibit milk secretion in females.

It is not known whether rasagiline is excreted in human milk. Because many drugs are excreted in human milk, caution should be exercised when AZILECT is administered to a nursing woman.

8.4 Pediatric Use

The safety and effectiveness of AZILECT in the pediatric population have not been studied.

8.5 Geriatric Use

Approximately half of patients in clinical trials were 65 years and over. There were no significant differences in the safety profile of the geriatric and non-geriatric patients.

8.6 Hepatic Impairment

Rasagiline plasma concentration may be increased in patients with mild (up to 2 fold, Child-Pugh score 5-6), moderate (up to 7 fold, Child-Pugh score 7-9), and severe (Child-Pugh score 10-15) hepatic impairment. Patients with mild hepatic impairment should be given the dose of 0.5 mg/day. AZILECT should not be used in patients with moderate or severe hepatic impairment [see Dosage and Administration (2.3), Warnings and Precautions (5.3) and Clinical Pharmacology (12.3)].

8.7 Renal Impairment

Dose adjustment of AZILECT is not required for patients with mild or moderate renal impairment because AZILECT plasma concentrations are not increased in patients with moderate renal impairment. Rasagiline has not been studied in patients with severe renal impairment.

9 DRUG ABUSE AND DEPENDENCE

Enter section text here

9.1 Controlled Substance

AZILECT is not a controlled substance.

9.2 Abuse

Studies conducted in mice and rats did not reveal any potential for drug abuse and dependence. Clinical trials have not revealed any evidence of the potential for abuse, tolerance or physical dependence; however, systematic studies in humans designed to evaluate these effects have not been performed.

9.3 Dependence

Studies conducted in mice and rats did not reveal any potential for drug abuse and dependence. Clinical trials have not revealed any evidence of the potential for abuse, tolerance or physical dependence; however, systematic studies in humans designed to evaluate these effects have not been performed.

10 OVERDOSAGE

No cases of AZILECT overdose were reported in clinical trials.

Rasagiline was well tolerated in a single-dose study in healthy volunteers receiving 20 mg/day and in a ten-day study in healthy volunteers receiving 10 mg/day. Adverse events were mild or moderate. In a dose escalation study in patients on chronic levodopa therapy treated with 10 mg of rasagiline there were three reports of cardiovascular side effects (including hypertension and postural hypotension) which resolved following treatment discontinuation.

Symptoms of overdosage, although not observed with rasagiline during clinical development, may resemble those observed with non-selective MAO inhibitors (MAOIs).

Although no cases of overdose have been observed with rasagiline during the clinical development program, the following description of presenting symptoms and clinical course is based upon overdose descriptions of non-selective MAO inhibitors.

Characteristically, signs and symptoms of non-selective MAOI overdose may not appear immediately. Delays of up to 12 hours between ingestion of drug and the appearance of signs may occur. Importantly, the peak intensity of the syndrome may not be reached for upwards of a day following the overdose. Death has been reported following overdosage. Therefore, immediate hospitalization, with continuous patient observation and monitoring for a period of at least two days following the ingestion of such drugs in overdose, is strongly recommended.

The clinical picture of MAOI overdose varies considerably; its severity may be a function of the amount of drug consumed. The central nervous and cardiovascular systems are prominently involved.

Signs and symptoms of overdosage may include, alone or in combination, any of the following: drowsiness, dizziness, faintness, irritability, hyperactivity, agitation, severe headache, hallucinations, trismus, opisthotonos, convulsions, and coma; rapid and irregular pulse, hypertension, hypotension and vascular collapse; precordial pain, respiratory depression and failure, hyperpyrexia, diaphoresis, and cool, clammy skin.

There is no specific antidote for rasagiline overdose. The following suggestions are offered based upon the assumption that rasagiline overdose may be modeled after non-selective MAO inhibitor poisoning. Treatment of overdose with non-selective MAO inhibitors is symptomatic and supportive. Respiration should be supported by appropriate measures, including management of the airway, use of supplemental oxygen, and mechanical ventilatory assistance, as required. Body temperature should be monitored closely. Intensive management of hyperpyrexia may be required. Maintenance of fluid and electrolyte balance is essential. For this reason, in cases of overdose with AZILECT, dietary tyramine restriction should be observed for several weeks to avoid the risk of a hypertensive/cheese reaction.

A poison control center should be called for the most current treatment guidelines.

A post-marketing report described a single patient who developed a non-fatal serotonin syndrome after ingesting 100 mg of AZILECT in a suicide attempt. Another patient who was treated in error with 4 mg AZILECT daily and tramadol also developed a serotonin syndrome. One patient who was treated in error with 3 mg AZILECT daily experienced alternating episodes of vascular fluctuations consisting of hypertension and orthostatic hypotension.

11 DESCRIPTION

AZILECT® tablets contain rasagiline (as the mesylate), a propargylamine-based drug indicated for the treatment of idiopathic Parkinson's disease. It is designated chemically as: 1H-Inden-1-amine, 2, 3-dihydro-N-2-propynyl-, (1R)-, methanesulfonate. The empirical formula of rasagiline mesylate is (C12H13N)CH4SO3 and its molecular weight is 267.34.

Its structural formula is:

Rasagiline mesylate is a white to off-white powder, freely soluble in water or ethanol and sparingly soluble in isopropanol. Each AZILECT tablet for oral administration contains rasagiline mesylate equivalent to 0.5 mg or 1 mg of rasagiline base.

Each AZILECT tablet also contains the following inactive ingredients: mannitol, starch, pregelatinized starch, colloidal silicon dioxide, stearic acid and talc.

12 CLINICAL PHARMACOLOGY

Enter section text here

12.1 Mechanism of Action

AZILECT functions as a selective, irreversible MAO-B inhibitor indicated for the treatment of idiopathic Parkinson's disease. The results of a clinical trial designed to examine the effects of Azilect on blood pressure when it is administered with increasing doses of tyramine indicates the functional selectivity can be incomplete when healthy subjects ingest large amounts of tyramine while receiving recommended doses of AZILECT. The selectivity for inhibiting MAO-B diminishes in a dose-related manner.

MAO, a flavin-containing enzyme, is classified into two major molecular species, A and B, and is localized in mitochondrial membranes throughout the body in nerve terminals, brain, liver and intestinal mucosa. MAO regulates the metabolic degradation of catecholamines and serotonin in the CNS and peripheral tissues. MAO-B is the major form in the human brain. In ex vivo animal studies in brain, liver and intestinal tissues, rasagiline was shown to be a potent, irreversible monoamine oxidase type B (MAO-B) selective inhibitor. Rasagiline at the recommended therapeutic dose was also shown to be a potent and irreversible inhibitor of MAO-B in platelets. The precise mechanisms of action of rasagiline are unknown. One mechanism is believed to be related to its MAO-B inhibitory activity, which causes an increase in extracellular levels of dopamine in the striatum. The elevated dopamine level and subsequent increased dopaminergic activity are likely to mediate rasagiline's beneficial effects seen in models of dopaminergic motor dysfunction.

12.2 Pharmacodynamics

Platelet MAO Activity in Clinical Studies

Studies in healthy subjects and in Parkinson's disease patients have shown that rasagiline inhibits platelet MAO-B irreversibly. The inhibition lasts at least 1 week after last dose. Almost 25-35% MAO-B inhibition was achieved after a single rasagiline dose of 1 mg/day and more than 55% of MAO-B inhibition was achieved after a single rasagiline dose of 2 mg/day. Over 90% inhibition was achieved 3 days after rasagiline daily dosing at 2 mg/day and this inhibition level was maintained 3 days post-dose. Multiple doses of rasagiline of 0.5, 1 and 2 mg per day resulted in complete MAO-B inhibition.

12.3 Pharmacokinetics

Rasagiline in the range of 1-6 mg demonstrated a more than proportional increase in AUC, while Cmax was dose proportional. Rasagiline mean steady-state half life is 3 hours but there is no correlation of pharmacokinetics with its pharmacological effect because of its irreversible inhibition of MAO-B.

Absorption

Rasagiline is rapidly absorbed, reaching peak plasma concentration (Cmax) in approximately 1 hour. The absolute bioavailability of rasagiline is about 36%.

Food does not affect the Tmax of rasagiline, although Cmax and exposure (AUC) are decreased by approximately 60% and 20%, respectively, when the drug is taken with a high fat meal. Because AUC is not significantly affected, AZILECT can be administered with or without food [see Dosage and Administration (2)].

Distribution

The mean volume of distribution at steady-state is 87 L, indicating that the tissue binding of rasagiline is in excess of plasma protein binding. Plasma protein binding ranges from 88-94% with mean extent of binding of 61-63% to human albumin over the concentration range of 1-100 ng/mL.

Metabolism and Elimination

Rasagiline undergoes almost complete biotransformation in the liver prior to excretion. The metabolism of rasagiline proceeds through two main pathways: N-dealkylation and/or hydroxylation to yield 1-aminoindan (AI), 3-hydroxy-N-propargyl-1 aminoindan (3-OH-PAI) and 3-hydroxy-1-aminoindan (3-OH-AI). In vitro experiments indicate that both routes of rasagiline metabolism are dependent on the cytochrome P450 (CYP) system, with CYP1A2 being the major isoenzyme involved in rasagiline metabolism. Glucuronide conjugation of rasagiline and its metabolites, with subsequent urinary excretion, is the major elimination pathway.

After oral administration of ^14C-labeled rasagiline, elimination occurred primarily via urine and secondarily via feces (62% of total dose in urine and 7% of total dose in feces over 7 days), with a total calculated recovery of 84% of the dose over a period of 38 days. Less than 1% of rasagiline was excreted as unchanged drug in urine.

Special Populations

Hepatic Impairment

Following repeat dose administration (7 days) of rasagiline (1 mg/day) in subjects with mild hepatic impairment (Child-Pugh score 5-6), AUC and Cmax were increased by 2 fold and 1.4 fold, respectively, compared to healthy subjects. In subjects with moderate hepatic impairment (Child-Pugh score 7-9), AUC and Cmax were increased by 7 fold and 2 fold, respectively, compared to healthy subjects [see Dosage and Administration (2.3) and Warnings and Precautions (5.3)].

Renal Impairment

Following repeat dose administration (8 days) of rasagiline (1 mg/day) in subjects with moderate renal impairment, rasagiline exposure (AUC) was similar to rasagiline exposure in healthy subjects, while the major metabolite 1-AI exposure (AUC) was increased 1.5- fold in subjects with moderate renal impairment, compared to healthy subjects. Because 1-AI is not an MAO inhibitor, no dose adjustment is needed for patients with mild and moderate renal impairment. Data are not available for patients with severe renal impairment.

Elderly

Since age has little influence on rasagiline pharmacokinetics, it can be administered at the recommended dose in the elderly (≥ 65 years).

Pediatric

AZILECT has not been investigated in patients below 18 years of age.

Gender

The pharmacokinetic profile of rasagiline is similar in men and women.

Drug-Drug Interactions

Tyramine Effect

[see Dosage and Administration (2), Warnings and Precautions (5.4), and Drug Interactions (7.9)].

Levodopa

Data from population pharmacokinetic studies comparing rasagiline clearance in the presence and absence of levodopa have given conflicting results. Although there may be some increase in rasagiline blood levels in the presence of levodopa, the effect is modest and rasagiline dosing need not be modified in the presence of levodopa.

Effect of Other Drugs on the Metabolism of AZILECT

In vitro metabolism studies showed that CYP1A2 was the major enzyme responsible for the metabolism of rasagiline. There is the potential for inhibitors of this enzyme to alter AZILECT clearance when coadministered [see Dosage and Administration (2.5) and Warnings and Precautions (5.2)].

Ciprofloxacin: When ciprofloxacin, an inhibitor of CYP1A2, was administered to healthy volunteers (n=12) at 500 mg (BID) with rasagiline at 2 mg/day, the AUC of rasagiline increased by 83% and there was no change in the elimination half life [see Dosage and Administration (2.5) and Warnings and Precautions (5.2)].

Theophylline: Coadministration of rasagiline 1 mg/day and theophylline, a substrate of CYP1A2, up to 500 mg twice daily to healthy subjects (n=24) did not affect the pharmacokinetics of either drug.

Antidepressants: Severe CNS toxicity (occasionally fatal) associated with hyperpyrexia as part of a serotonin syndrome, has been reported with combined treatment of an antidepressant (e.g., from one of many classes including tricyclic or tetracyclic antidepressants, SSRIs, SNRIs, triazolopyridine antidepressants) and non-selective MAOI or a selective MAO-B inhibitor [see Warnings and Precautions (5.1)].

Effect of AZILECT on Other Drugs

No additional in vivo trials have investigated the effect of AZILECT on other drugs metabolized by the cytochrome P450 enzyme system. In vitro studies showed that rasagiline at a concentration of 1mcg/ml (equivalent to a level that is 160 times the average Cmax ~ 5.9-8.5 ng/mL in Parkinson's disease patients after 1 mg rasagiline multiple dosing) did not inhibit cytochrome P450 isoenzymes, CYP1A2, CYP2A6, CYP2C9, CYP2C19, CYP2D6, CYP2E1, CYP3A4 and CYP4A. These results indicate that rasagiline is unlikely to cause any clinically significant interference with substrates of these enzymes.

13 NONCLINICAL TOXICOLOGY

Enter section text here

13.1 Carcinogenesis, Mutagenesis, Impairment of Fertility

Carcinogenesis

Two year carcinogenicity studies were conducted in CD-1 mice at oral (gavage) doses of 1, 15, and 45 mg/kg and in Sprague-Dawley rats at oral (gavage) doses of 0.3, 1, and 3 mg/kg (males) or 0.5, 2, 5, and 17 mg/kg (females). In rats, there was no increase in tumors at any dose tested. Plasma exposures at the highest dose tested were approximately 33 and 260 times, in male and female rats, respectively, the expected plasma exposures in humans at the maximum recommended dose (MRD) of 1 mg/day.

In mice, there was an increase in lung tumors (combined adenomas/carcinomas) at 15 and 45 mg/kg males and females. Plasma exposures associated with the no-effect dose (1 mg/kg) were approximately 5 times those expected in humans at the MRD.

The carcinogenic potential of rasagiline administered in combination with levodopa/carbidopa has not been examined.

Mutagenesis

Rasagiline was reproducibly clastogenic in in vitro chromosomal aberration assays in human lymphocytes in the presence of metabolic activation and was mutagenic and clastogenic in the in vitro mouse lymphoma tk assay in the absence and presence of metabolic activation. Rasagiline was negative in the in vitro bacterial reverse mutation (Ames) assay, the in vivo unscheduled DNA synthesis assay, and the in vivo micronucleus assay in CD-1 mice. Rasagiline was also negative in the in vivo micronucleus assay in CD-1 mice when administered in combination with levodopa/carbidopa.

Impairment of Fertility

Rasagiline had no effect on mating performance or fertility in male rats treated prior to and throughout the mating period, or in female rats treated from prior to mating through day 17 of gestation at oral doses up to 3 mg/kg/day (approximately 30 times the expected plasma rasagiline exposure (AUC) at the maximum recommended human dose [1 mg/day]). The effect of rasagiline administered in combination with levodopa/carbidopa on mating and fertility has not been examined.

14 CLINICAL TRIALS

The effectiveness of AZILECT for the treatment of Parkinson's disease was established in three 18- to 26-week, randomized, placebo-controlled trials. In one of these trials AZILECT was given as initial monotherapy and in the other two as adjunctive therapy to levodopa.

14.1 Monotherapy Use of AZILECT

The monotherapy trial was a double-blind, randomized, fixed-dose parallel group, 26-week study in early Parkinson's disease patients not receiving any concomitant dopaminergic therapy at the start of the study. The majority of the patients were not treated with any anti-Parkinson's disease medication before receiving rasagiline treatment.

In this trial, 404 patients were randomly assigned to receive placebo (138 patients), rasagiline 1 mg/day (134 patients) or rasagiline 2 mg/day (132 patients). Patients were not allowed to take levodopa, dopamine agonists, selegiline or amantadine, but if necessary, could take stable doses of anticholinergic medication. The average Parkinson's disease duration was approximately 1 year (range 0 to 11 years).

The primary measure of effectiveness was the change from baseline in the total score of the Unified Parkinson's Disease Rating Scale (UPDRS), [mentation (Part I) + activities of daily living (ADL) (Part II) + motor function (Part III)]. The UPDRS is a multi-item rating scale that measures the ability of a patient to perform mental and motor tasks as well as activities of daily living. A reduction in the score represents improvement and a beneficial change from baseline appears as a negative number.

Rasagiline (1 or 2 mg once daily) had a significant beneficial effect relative to placebo on the primary measure of effectiveness in patients receiving six months of treatment and not on dopaminergic therapy. Patients who received rasagiline had significantly less worsening in the UPDRS score, compared to those who received placebo. The effectiveness of rasagiline 1 mg and 2 mg was comparable. Table 3 displays the results of the monotherapy trial.

Table 3. Parkinson's Disease Patients not on Dopaminergic Therapy (Monotherapy)
Primary Measure of Effectiveness: Change in total UPDRS score
 | Baseline score | Change from baseline to termination score | p-value vs. placebo
Placebo | 24.5 | 3.9 | ---
1.0 mg/day | 24.7 | 0.1 | 0.0001
2.0 mg/day | 25.9 | 0.7 | 0.0001

For the comparison between rasagiline 1 mg/day and placebo, no differences in effectiveness based on age or gender were detected.

14.2 Adjunctive use of AZILECT

Two multicenter, randomized, multinational trials were conducted in more advanced Parkinson's disease patients treated chronically with levodopa and experiencing motor fluctuations (including but not limited to, end of dose "wearing off," sudden or random "off," etc.). The first (Study 1) was conducted in North America (U.S. and Canada) and compared two doses (0.5 mg and 1 mg daily) of rasagiline and placebo while the second (Study 2) was conducted outside of North America (several European countries, Argentina, Israel) and studied only a single dose (1 mg daily) of rasagiline and placebo. Patients had had Parkinson's disease for an average of 9 years (range 5 months to 33 years), had been taking levodopa for an average of 8 years (range 5 months to 32 years), and had been experiencing motor fluctuations for approximately 3 to 4 years (range 1 month to 23 years). Patients kept home diaries just prior to baseline and at specified intervals during the trial. Diaries recorded one of the following four conditions for each half-hour interval over a 24-hour period: "ON" (period of relatively good function and mobility) as either "ON" with no dyskinesia or without troublesome dyskinesia, or "ON" with troublesome dyskinesia, "OFF" (period of relatively poor function and mobility) or asleep. "Troublesome" dyskinesia is defined as that which interferes with the patient's daily activity. All patients had been inadequately controlled and were experiencing motor fluctuations typical of advanced stage disease despite receiving levodopa/decarboxylase inhibitor. The average dose of levodopa/decarboxylase inhibitor was approximately 700 to 800 mg (range 150 to 3000 mg/day). Patients were also allowed to take stable doses of additional anti-PD medications at entry into the trials. In both trials, approximately 65% of patients were on dopamine agonists and in the North American study (Study 1) approximately 35% were on entacapone. The majority of patients taking entacapone were taking a dopamine agonist as well.

In both trials the primary measure of effectiveness was the change in the mean number of hours that were spent in the "OFF" state at baseline compared to the mean number of hours that were spent in the "OFF" state during the treatment period.

The first adjunct study (Study 1) was a double-blind, randomized, fixed-dose, parallel group trial conducted in 472 levodopa-treated Parkinson's disease patients who were experiencing motor fluctuations. Patients were randomly assigned to receive placebo (159 patients), rasagiline 0.5 mg/day (164 patients), or rasagiline 1 mg/day (149 patients), and were treated for 26 weeks. Patients averaged approximately 6 hours daily in the "OFF" state at baseline, as confirmed by home diaries.

The second adjunct study (Study 2) was a double-blind, randomized, parallel group trial conducted in 687 levodopa-treated Parkinson's disease patients who were experiencing motor fluctuations. Patients were randomly assigned to receive placebo (229 patients), rasagiline 1 mg/day (231 patients) or an active comparator, a COMT inhibitor taken along with scheduled doses of levodopa/decarboxylase inhibitor (227 patients). Patients were treated for 18 weeks. Patients averaged approximately 5.6 hours daily in the "OFF" state at baseline as confirmed by home diaries.

In both studies, rasagiline 1 mg once daily reduced "OFF" time compared to placebo when added to levodopa in patients experiencing motor fluctuations (Tables 4 and 5). The lower dose (0.5 mg) of rasagiline also significantly reduced "OFF" time (Table 4), but had a numerically smaller effect than the 1 mg dose of rasagiline. In Study 2, the active comparator also reduced "OFF" time when compared to placebo.

Table 4. Parkinson's Disease Patients Receiving AZILECT as Adjunct Therapy (Study 1)
Primary Measure of Effectiveness: Change in mean total daily "OFF" time
 | Baseline (hours) | Change from baseline to treatment period (hours) | p-value vs. placebo
Placebo | 6.0 | -0.9 | ---
0.5 mg/day | 6.0 | -1.4 | 0.0199
1.0 mg/day | 6.3 | -1.9 | <0.0001

Table 5. Parkinson's Disease Patients Receiving AZILECT as Adjunct Therapy (Study 2)
Primary Measure of Effectiveness: Change in mean total daily "OFF" time
 | Baseline (hours) | Change from baseline to treatment period (hours) | p-value vs. placebo
Placebo | 5.5 | -0.40 | ---
1.0 mg/day | 5.6 | -1.2 | 0.0001

In both studies, dosage reduction of levodopa was allowed within the first 6 weeks if dopaminergic side effects, including dyskinesia and hallucinations, emerged. In Study 1, levodopa dosage reduction occurred in 8% of patients in the placebo group and in 16% and 17% of patients in the 0.5 mg/day and 1 mg/day rasagiline groups, respectively. In those patients who had levodopa dosage reduced, the dose was reduced on average by about 7%, 9%, and 13% in the placebo, 0.5 mg/day, and 1 mg/day groups, respectively. In Study 2, levodopa dosage reduction occurred in 6% of patients in the placebo group and in 9% in the rasagiline 1 mg/day group. In patients who had their levodopa dosage reduced, the dose was reduced on average by about 13% and 11% in the placebo and the rasagiline groups, respectively.

For the comparison between rasagiline 1 mg/day and placebo in both studies, no differences in effectiveness based on age or gender were detected.

Several secondary outcome assessments in the two studies showed statistically significant improvements with rasagiline. These included effects on the activities of daily living (ADL) subscale of the UPDRS performed during an "OFF" period and the motor subscale of the UPDRS performed during an "ON" period. In both scales, a negative response represents improvement. Tables 6 and 7 show these results for Studies 1 and 2.

Table 6. Secondary Measures of Effectiveness (Study 1)
 | Baseline (score) | Change from baseline to last value
UPDRS ADL (Activities of Daily Living) subscale score while "OFF"
Placebo | 15.5 | 0.68
0.5 mg/day | 15.8 | -0.60
1.0 mg/day | 15.5 | -0.68
UPDRS Motor subscale score while "ON"
Placebo | 20.8 | 1.21
0.5 mg/day | 21.5 | -1.43
1.0 mg/day | 20.9 | 1/30

Table 7. Secondary Measures of Effectiveness (Study 2)
 | Baseline (score) | Change from baseline to last value
UPDRS ADL (Activities of Daily Living) subscale score while "OFF"
Placebo | 18.7 | -0.89
1.0 mg/day | 19.0 | -2.61
UPDRS Motor subscale score while "ON"
Placebo | 23.5 | -0.82
1.0 mg/day | 23.8 | -3.87

16 HOW SUPPLIED

AZILECT 1 mg Tablets:

White to off-white, round, flat, beveled tablets, debossed with "GIL 1" on one side and plain on the other side.

Supplied as bottles of 30 tablets (NDC 54868-6206-0).

Storage:

Store at 25°C (77°F) with excursions permitted to 15°-30°C (59°-86°F).

17 INFORMATION FOR PATIENTS

Enter section text here

17.1 Coadministration of Antidepressants and Other Drugs

Patients should inform their physician if they are taking, or planning to take, any prescription or over-the-counter drugs, especially antidepressants and over-the-counter cold medications, since there is a potential for interaction with AZILECT. Because patients should not use meperidine or certain other analgesics with AZILECT, they should contact their healthcare provider before taking analgesics [see Warnings and Precautions (5.1)].

17.2 Ciprofloxacin or Other CYP1A2 Inhibitors

Patients should be informed that they should contact their healthcare provider of AZILECT if they take ciprofloxacin or a similar drug that could increase blood levels of rasagiline because of the need to adjust the dose of AZILECT [see Warnings and Precautions (5.2)].

17.3 Risk of Hypertensive Crisis and Nonselective Monoamine Oxidase Inhibition Above the Recommended Doses

Patients should be advised not to exceed the maximum recommended daily dose of 1 mg/day (0.5 mg/day for subjects with mild hepatic impairment and subjects using concomitant ciprofloxacin and other CYP1A2 inhibitors).

The risk of using higher than recommended daily doses of AZILECT should be explained, and a brief description of the hypertensive/cheese reaction provided.

The possibility exists that very tyramine-rich foods (e.g., aged cheese such as Stilton) could possibly cause an increase in blood pressure. Patients should be advised to avoid certain foods (e.g., aged cheese) containing a very large amount of tyramine while taking recommended doses of AZILECT because of the potential for large increases in blood pressure. If patients eat foods very rich in tyramine and do not feel well soon after eating, they should contact their healthcare provider [see Warnings and Precautions (5.4)].

17.4 Melanoma

It is not known if melanoma is associated with Parkinson's disease or the medicines used to treat Parkinson's disease. Patients being treated with AZILECT should be advised to have periodic skin examinations. [see Warnings and Precautions (5.5)].

17.5 Dyskinesia

Patients taking AZILECT as adjunct to levodopa should be advised that there is a possibility of dyskinesia or increased dyskinesia [see Warnings and Precautions (5.6)].

17.6 Lowering of Blood Pressure and Postural/Orthostatic Hypotension

Patients should be advised that they may develop postural (orthostatic) hypotension with or without symptoms such as dizziness, nausea, syncope, and sometimes sweating. Hypotension and/or orthostatic symptoms may occur more frequently during initial therapy or with an increase in dose at any time (cases have been seen after weeks of treatment). Accordingly, patients should be cautioned against standing up rapidly after sitting or lying down, especially if they have been doing so for prolonged periods, and especially, at the initiation of treatment with AZILECT [see Warnings and Precautions (5.7)].

17.7 Elevation of Blood Pressure

Patients should be alerted to the possibility of increases in blood pressure during treatment with AZILECT. Exacerbation of hypertension may occur. Medication dose adjustment may be necessary if elevation of blood pressure is sustained over multiple evaluations [see Warnings and Precautions (5.8)].

17.8 Hallucinations / Psychotic-Like Behavior

Patients should be informed that hallucinations or other manifestations of psychotic-like behavior can occur when taking AZILECT. Patients should also be advised that, if they have a major psychotic disorder, that AZILECT should not ordinarily be used because of the risk of exacerbating the psychosis. Patients with a major psychotic disorder should also be aware that many treatments for psychosis may decrease the effectiveness of AZILECT [see Warnings and Precautions (5.9)].

17.9 Withdrawal-Emergent Hyperpyrexia and Confusion

Patients should be told to contact their healthcare provider if they wish to discontinue Azilect.

17.10 Missing Dose

Patients should be instructed to take AZILECT as prescribed. If a dose is missed, the patient should not double-up the dose of AZILECT. The next dose should be taken at the usual time on the following day.

17.11 Impulse Control / Compulsive Behaviors

There have been reports of patients experiencing intense urges to gamble, increased sexual urges, other intense urges, and the inability to control these urges while taking one or more of the medications that increase central dopaminergic tone and that are generally used for the treatment of Parkinson's disease (including AZILECT). Although it is not proven that the medications caused these events, these urges were reported to have stopped in some cases when the dose was reduced or the medication was stopped. Prescribers should ask patients about the development of new or increased gambling urges, sexual urges, or other urges while being treated with rasagiline. Patients should inform their physician if they experience new or increased gambling urges, increased sexual urges, or other intense urges while taking rasagiline. Physicians should consider dose reduction or stopping the medication if a patient develops such urges while taking rasagiline.

U.S. Patent Nos. 5387612, 5453446, 5457133, 5532415, 5786390, 6126968

Marketed by: TEVA Neuroscience, Inc., Kansas City, MO 64131
Distributed by: TEVA Pharmaceuticals USA, Inc., North Wales, PA 19454
Product of Israel

Relabeling of "Additional Barcode Label" by:
Physicians Total Care, Inc.
Tulsa, OK 74146

PRINCIPAL DISPLAY PANEL

AZILECT®
(rasagiline tablets)
1 mg
30 Tablets Rx only